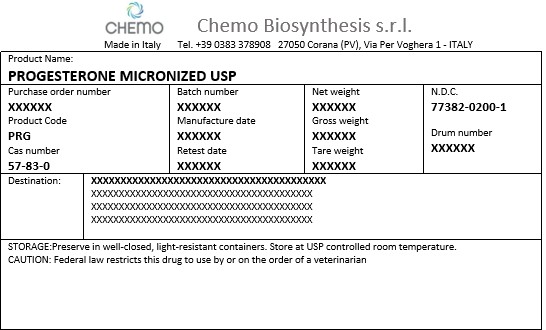 DRUG LABEL: Progesterone Micronized
NDC: 77382-0200 | Form: POWDER
Manufacturer: Chemo Biosynthesis srl
Category: other | Type: BULK INGREDIENT - ANIMAL DRUG
Date: 20251218

ACTIVE INGREDIENTS: PROGESTERONE 1 kg/1 kg

Progesterone Micronized USP